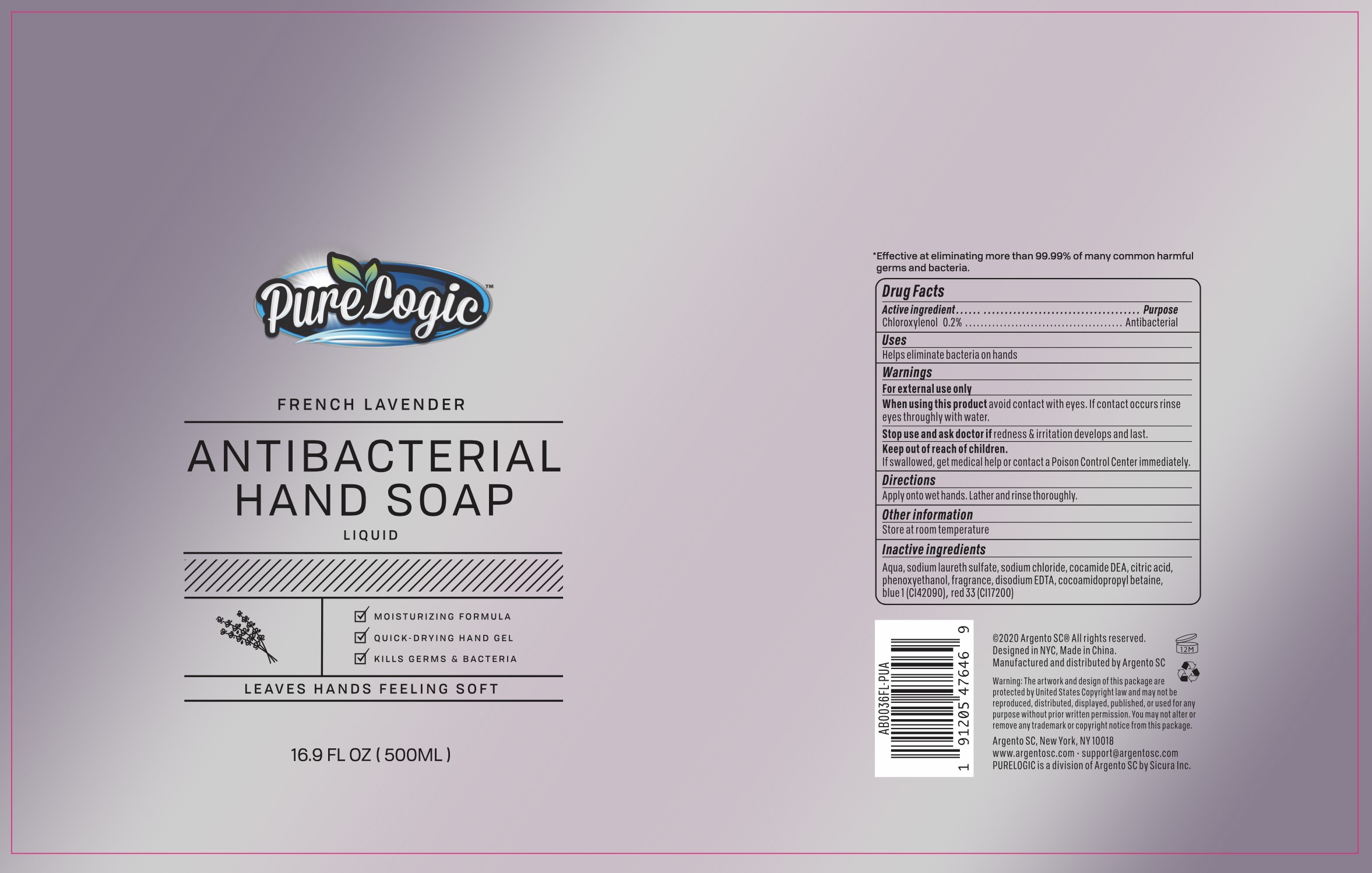 DRUG LABEL: PureLogic French Lavender Antibacterial Hand
NDC: 77731-062 | Form: SOAP
Manufacturer: Argento sc by sicura inc.
Category: otc | Type: HUMAN OTC DRUG LABEL
Date: 20200901

ACTIVE INGREDIENTS: CHLOROXYLENOL 0.2 g/100 mL
INACTIVE INGREDIENTS: SODIUM LAURETH SULFATE; SODIUM CHLORIDE; WATER; FD&C BLUE NO. 1; COCAMIDOPROPYL BETAINE; CITRIC ACID MONOHYDRATE; PHENOXYETHANOL; DISODIUM HEDTA; D&C RED NO. 33

AB0036FL soap 2

Active Ingredient(s)

Chloroxylenol 0.2%

Purpose:

Antibacterial

Use

Helps eliminate bacteria on hands

Warnings

For external use only

When using this product, avoid contact with eyes. If contact occurs, rinse eyes thoroughly with water

Stop use and ask a doctor

if redness and irrigation develop and last

Keep out of reach of children

if swallowed, get medical help or contact a Poison Control Center immediately

Directions

Apply onto wet hands. Lather and rinse thoroughly

Other information

Store at room temperature

Inactive ingredients

Water, Sodium Laureth Sulfate, Cocamide DEA, Citric Acid, Phenoxyethanol, Fragrance, Cocamidopropyl betaine, Disodium EDTA, Blue 1 (CI42090), Red 33 (CI17200)